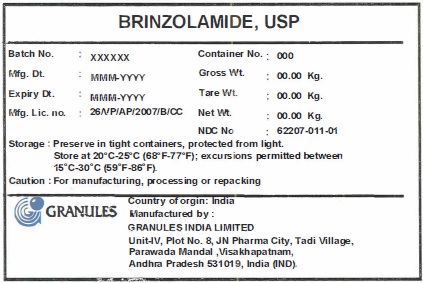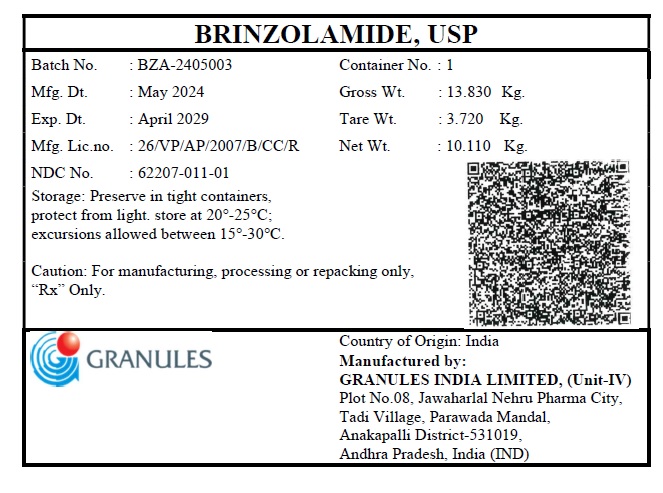 DRUG LABEL: Brinzolamide
NDC: 62207-011 | Form: POWDER
Manufacturer: Granules India Limited
Category: other | Type: BULK INGREDIENT
Date: 20251024

ACTIVE INGREDIENTS: BRINZOLAMIDE 25 kg/1 1

Brinzolamide